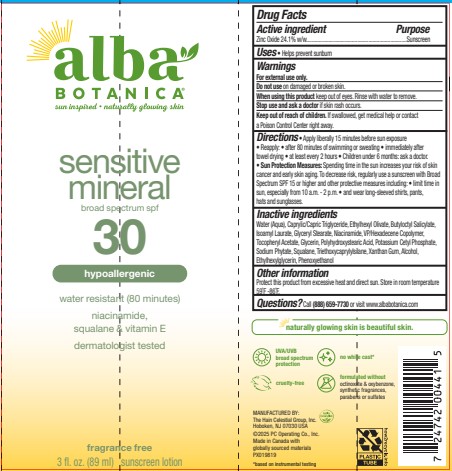 DRUG LABEL: Alba Botanica Sensitive Mineral SPF 30
NDC: 61995-2034 | Form: LOTION
Manufacturer: The Hain Celestial Group, Inc.
Category: otc | Type: HUMAN OTC DRUG LABEL
Date: 20251126

ACTIVE INGREDIENTS: ZINC OXIDE 24.1 g/100 g
INACTIVE INGREDIENTS: BUTYLOCTYL SALICYLATE; VINYLPYRROLIDONE/HEXADECENE COPOLYMER; GLYCERYL STEARATE; ISOAMYL LAURATE; NIACINAMIDE; POLYHYDROXYSTEARIC ACID (2300 MW); SQUALANE; ETHYLHEXYLGLYCERIN; POTASSIUM CETYL PHOSPHATE; WATER; PHENOXYETHANOL; GLYCERIN; .ALPHA.-TOCOPHEROL ACETATE; XANTHAN GUM; ETHYLHEXYL OLIVATE; ALCOHOL; CAPRYLIC/CAPRIC TRIGLYCERIDE; SODIUM PHYTATE; TRIETHOXYCAPRYLYLSILANE

AL00441 Alba Botanica Sensitive Mineral SPF 30
Formula PF163046-09

ACTIVE INGREDIENT

Zinc Oxide 24.1% (w/w)

DOSAGE AND ADMINISTRATION

Apply liberally 15 minutes before sun exposure. Reapply: ● after 80 minutes of swimming or sweating ● immediately after towel drying ● at least every 2 hours. Children under 6 months of age: ask a doctor.

PURPOSE

Sunscreen

WARNINGS

For external use only. Do not use on damaged or broken skin. When using this product keep out of eyes. Rinse with water to remove. Stop use and ask a doctor if skin rash occurs.

Keep out of reach of children. If swallowed get medical help or contact Poison Center right away.

INACTIVE INGREDIENT

Water (Aqua), Caprylic/Capric Triglyceride, Ethylhexyl Olivate, Butyloctyl Salicylate, Isoamyl Laurate, Glyceryl Stearate, Niacinamide, VP/Hexadecene Copolymer, Tocopheryl Acetate, Glycerin, Polyhydroxystearic Acid, Potassium Cetyl Phosphate, Sodium Phytate, Squalane, Triethoxycaprylylsilane, Xanthan Gum, Alcohol, Ethylhexylglycerin, Phenoxyethanol

INDICATIONS AND USAGE

Helps prevents sunburns. If used as directed with other sun protection measures, decreases risk of skin cancer and early skin aging caused by sun exposure. Skin Protection Measures: Spending time in the sun increases your risk of skin cancer and early skin aging. To decrease risk, regularly use sunscreen with Broad Spectrum SPF 15 or higher and other protective measures including: limit time in sun, especially from10am to 2pm, and wear long sleeved shirts, pants, hats and sunglases.